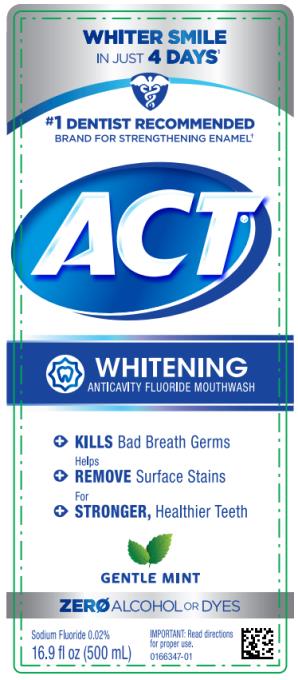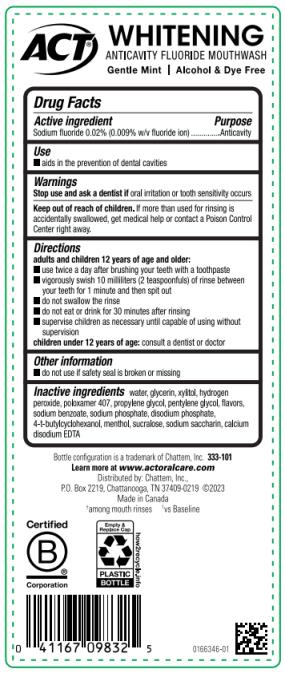 DRUG LABEL: ACT Whitening Anticavity Gentle Mint
NDC: 41167-0983 | Form: MOUTHWASH
Manufacturer: Chattem, Inc.
Category: otc | Type: HUMAN OTC DRUG LABEL
Date: 20240701

ACTIVE INGREDIENTS: SODIUM FLUORIDE 0.09 mg/1 mL
INACTIVE INGREDIENTS: WATER; GLYCERIN; XYLITOL; HYDROGEN PEROXIDE; POLOXAMER 407; PROPYLENE GLYCOL; PENTYLENE GLYCOL; SODIUM BENZOATE; SODIUM PHOSPHATE; SODIUM PHOSPHATE, DIBASIC, ANHYDROUS; 4-TERT-BUTYLCYCLOHEXANOL; MENTHOL; SUCRALOSE; SACCHARIN SODIUM; EDETATE CALCIUM DISODIUM ANHYDROUS

ACT Whitening Anticavity Fluoride Mouthwash Gentle Mint

ACT Whitening

Anticavity Gentle Mint

Drug Facts

Active ingredient

Sodium fluoride 0.02% (0.009% w/v fluoride ion)

Purpose

Anticavity

Use

■ aids in the prevention of dental cavities

Warnings

Stop use and ask a dentist if

oral irritation or tooth sensitivity occurs

Keep out of reach of children.

If more than used for rinsing is accidentally swallowed, get medical help or contact a Poison Control Center right away.

Directions

adults and children 12 years of age and older:

■ use twice a day after brushing your teeth with a toothpaste

■ vigorously swish 10 milliliters (2 teaspoonfuls) of rinse between your teeth for 1 minute and then spit out

■ do not swallow the rinse

■ do not eat or drink for 30 minutes after rinsing

■ supervise children as necessary until capable of using without supervision

children under 12 years of age: consult a dentist or doctor

Other information

■ do not use if safety seal is broken or missing

Inactive ingredients

water, glycerin, xylitol, hydrogen peroxide, poloxamer 407, propylene glycol, pentylene glycol, flavors, sodium benzoate, sodium phosphate, disodium phosphate, 4-t-butylcyclohexanol, menthol, sucralose, sodium saccharin, calcium disodium EDTA

PRINCIPAL DISPLAY PANEL

ACT
WHITENING
ANTICAVITY FLUORIDE MOUTHWASH
GENTLE MINT
16.9 fl oz (500 mL)